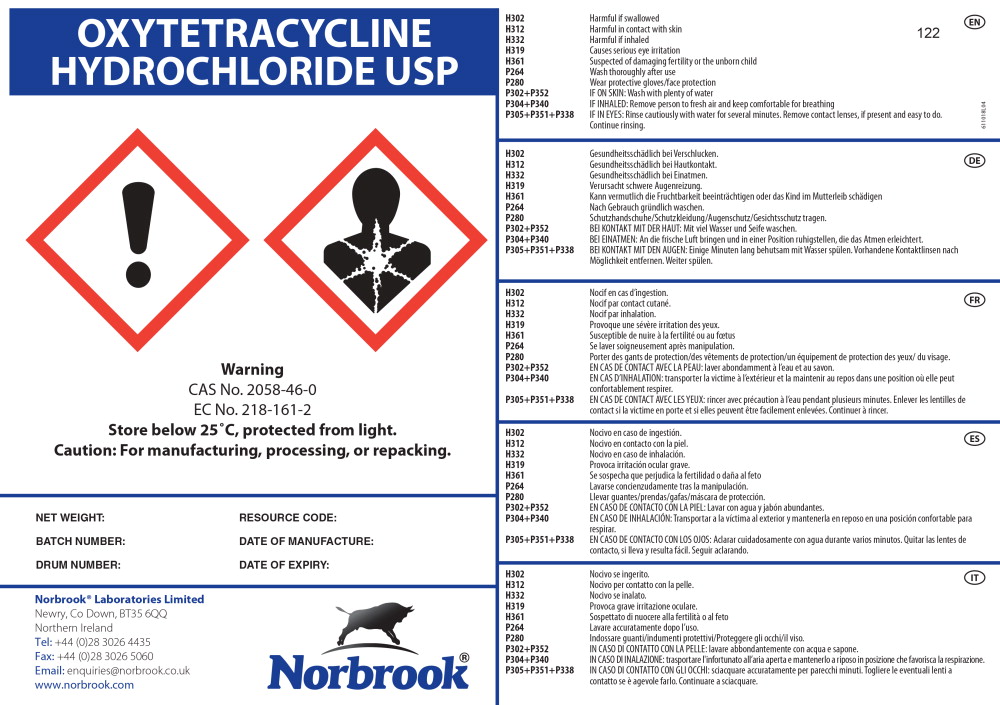 DRUG LABEL: Oxytetracycline Hydrochloride
NDC: 55529-660 | Form: POWDER
Manufacturer: Norbrook Laboratories Limited
Category: other | Type: BULK INGREDIENT - ANIMAL DRUG
Date: 20170509

ACTIVE INGREDIENTS: Oxytetracycline Hydrochloride 1 kg/1 kg

Principal Display Panel - Oxytetracycline Hydrochloride Bulk Drum Label

OXYTETRACYCLINE
HYDROCHLORIDE USP

Warning

CAS No. 2058-46-0

EC No. 218-161-2

Store below 25˚C, protected from light.

Caution: For manufacturing, processing, or repacking.

NET WEIGHT: RESOURCE CODE:

BATCH NUMBER: DATE OF MANUFACTURE:

DRUM NUMBER: DATE OF EXPIRY:

Norbrook® Laboratories Limited

Newry, Co Down, BT35 6QQ

Northern Ireland

Tel: +44 (0)28 3026 4435

Fax: +44 (0)28 3026 5060

Email: enquiries@norbrook.co.uk

www.norbrook.com